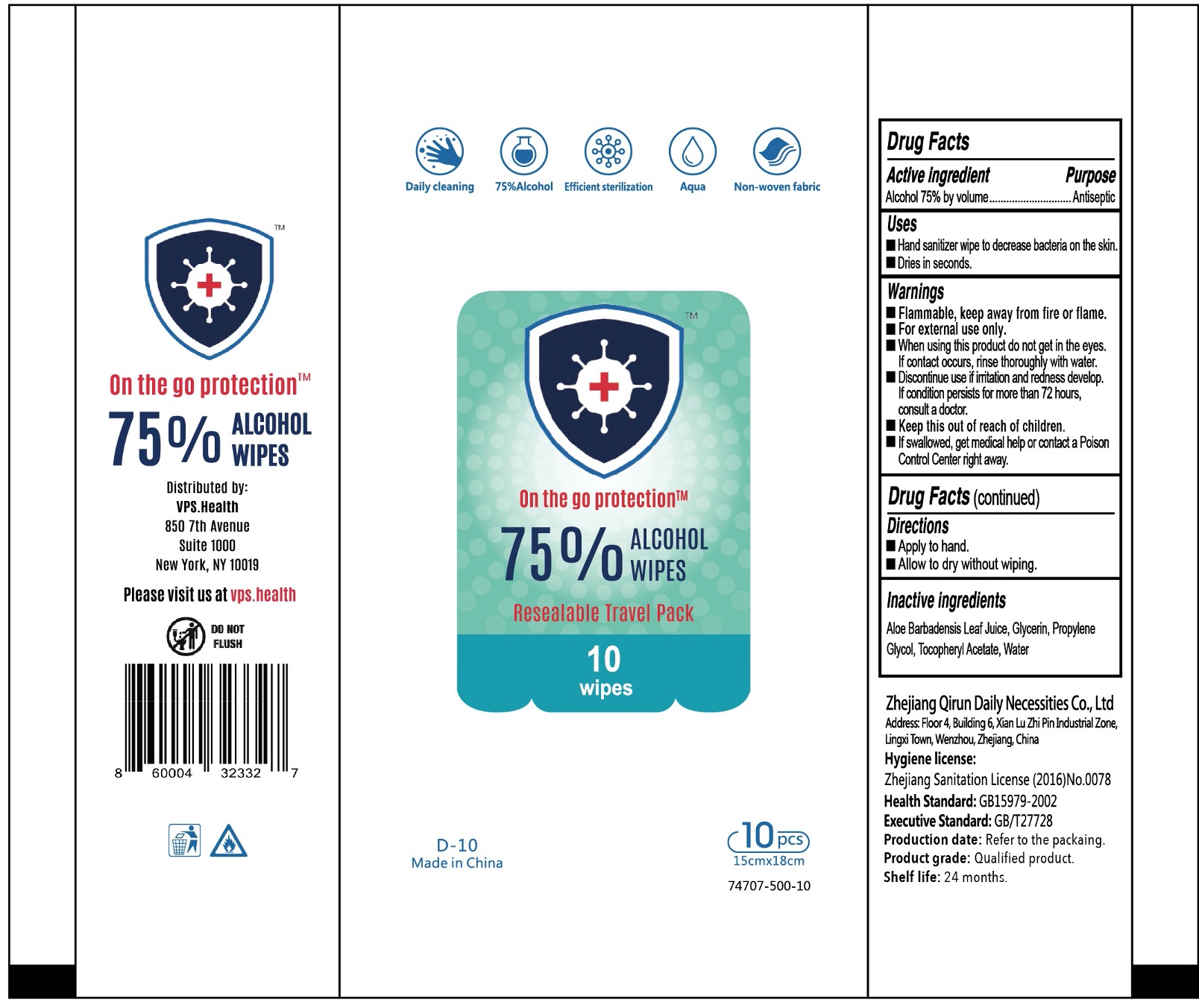 DRUG LABEL: Alchohol Wipes
NDC: 74707-500 | Form: CLOTH
Manufacturer: Virus Protection Systems LLC
Category: otc | Type: HUMAN OTC DRUG LABEL
Date: 20200813

ACTIVE INGREDIENTS: ALCOHOL 75 g/100 g
INACTIVE INGREDIENTS: WATER O-15 25 g/100 g

Disinfectant Sanitary Alcohol Wipes

Acohol 75% by Volume

Alcohol 75% by volume........Antispetic

WARNINGS SECTION

Flammable keep away from flame and fire

For external use only

When using this product do not get in the eyes, if contact occurs rinse throughly with water

Dicontinue use if irritaton and redeness devvelop.If conditions persist for more than 72 hours consult a doctor

keep this out of reach of children

if swallowed, get medical help or contact a poison control center right away

USES SECTION

Hand Sanitizer Wipe to decrease bacteria on the skin

Dries in Seconds

Directions

Apply to hand

Allow to dry without wiping

INACTIVE INGREDIENT

Aloe Barbadensis Leaf Juice

Glycerin

Propylene

Glycol

Tocopheryl

Water

DOSAGE AND ADMINISTRATION

Apply to hands

Aplly tyo dry without wiping

INDICATIONS AND USAGE

Hand Sanitizer wipe to decrease bacteria on the skin

Dries in seconds

keep this out of reach of children